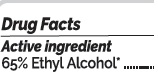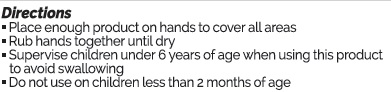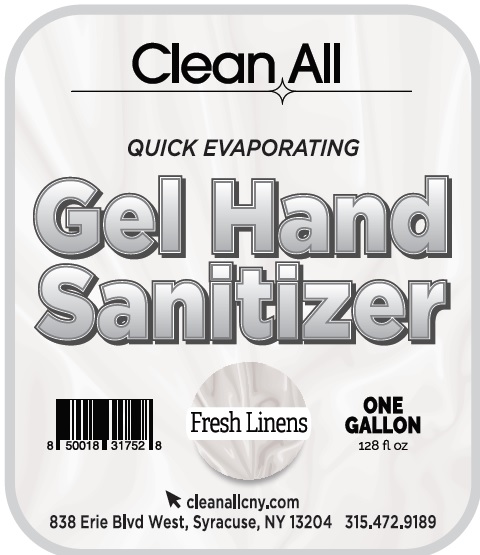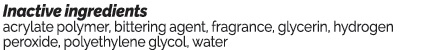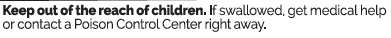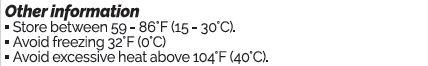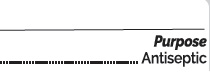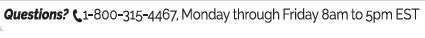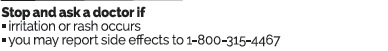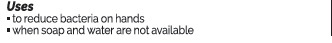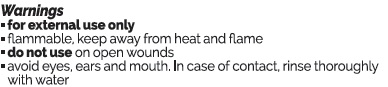 DRUG LABEL: Clean All Gel Hand Sanitizer Fresh Linen
NDC: 75660-134 | Form: GEL
Manufacturer: Solvents and Petroleum Inc
Category: otc | Type: HUMAN OTC DRUG LABEL
Date: 20201014

ACTIVE INGREDIENTS: ALCOHOL 65 mL/100 mL
INACTIVE INGREDIENTS: DENATONIUM BENZOATE 0.01 mL/100 mL; FRAGRANCE LINEN ORC1900779 0.01 mL/100 mL; GLYCERIN 1.35 mL/100 mL; HYDROGEN PEROXIDE 0.18 mL/100 mL; WATER 30.95 mL/100 mL; POLYETHYLENE GLYCOL, UNSPECIFIED 2 mL/100 mL; ACRYLATES/VINYL ISODECANOATE CROSSPOLYMER (10000 MPA.S NEUTRALIZED AT 0.5%) 0.5 mL/100 mL

Fresh Linen Scented Clean All Gel Hand Sanitizer

Active Ingredient(s)

Alcohol 65%

Purpose

Antiseptic, Hand Sanitizer

Use

to reduce bacteria on hands. For use when soap and water are not available.

Warnings

For external use only. Flammable. Keep away from heat or flame. do not use on open wounds, avoid eyes ears and mouth. in case of contact, rinse thoroughly with water.

Stop use and ask doctor

Stop use and ask a doctor if irritation or rash occurs

you may report side effects to 1-800-315-4467

Keep out of reach of children. If swallowed, get medical help or contact a Poison Control Center right away.

Directions

- Place enough product on hands to cover all surfaces. Rub hands together until dry.
- Supervise children under 6 years of age when using this product to avoid swallowing.
- Do not use on children less than 2 months of age

Other information

- Store between 15-30C (59-86F)
- Avoid freezing and excessive heat above 40C (104F)

Inactive ingredients

acrylate polymer, bittering agent, fragrance, glycerin, hydrogen peroxide, polyethylene glycol, water

Questions

1-800-315-4467, Monday through Friday 8am to 5pm EST